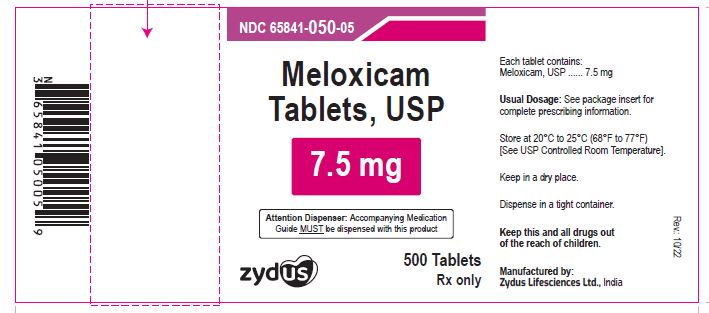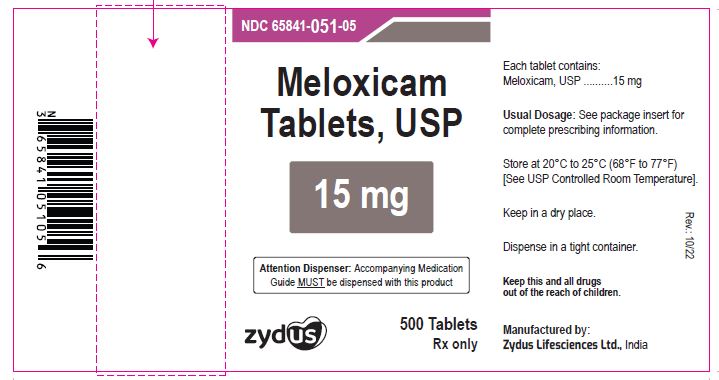 DRUG LABEL: meloxicam
NDC: 65841-050 | Form: TABLET
Manufacturer: Zydus Lifesciences Limited
Category: prescription | Type: HUMAN PRESCRIPTION DRUG LABEL
Date: 20241130

ACTIVE INGREDIENTS: MELOXICAM 7.5 mg/1 1
INACTIVE INGREDIENTS: CROSPOVIDONE (15 MPA.S AT 5%); LACTOSE MONOHYDRATE; MAGNESIUM STEARATE; MICROCRYSTALLINE CELLULOSE 101; POVIDONE K30; SILICON DIOXIDE; TRISODIUM CITRATE DIHYDRATE

MELOXICAM TABLETS

SPL MEDGUIDE

Manufactured by:

Cadila Healthcare Ltd.

India.

PACKAGE LABEL.PRINCIPAL DISPLAY PANEL

NDC 65841-050-01 in bottle of 500 tablets

Meloxicam Tablets USP, 7.5 mg

Rx only

500 tablets

NDC 65841-051-01 in bottle of 500 tablets

Meloxicam Tablets USP, 15 mg

Rx only

500 tablets